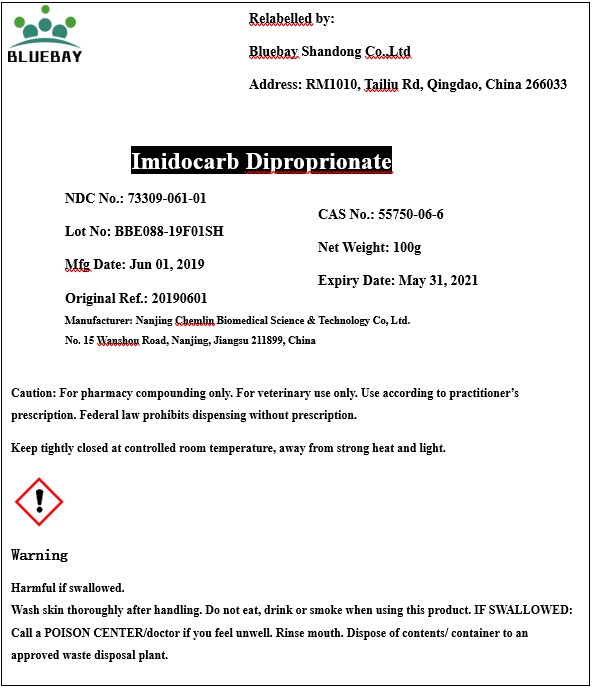 DRUG LABEL: imidocarb dipropionate
NDC: 73309-061 | Form: POWDER
Manufacturer: BLUEBAY SHANDONG CO.,LTD
Category: other | Type: BULK INGREDIENT
Date: 20191129

ACTIVE INGREDIENTS: IMIDOCARB DIPROPIONATE 1 g/1 g

imidocarb dipropionate